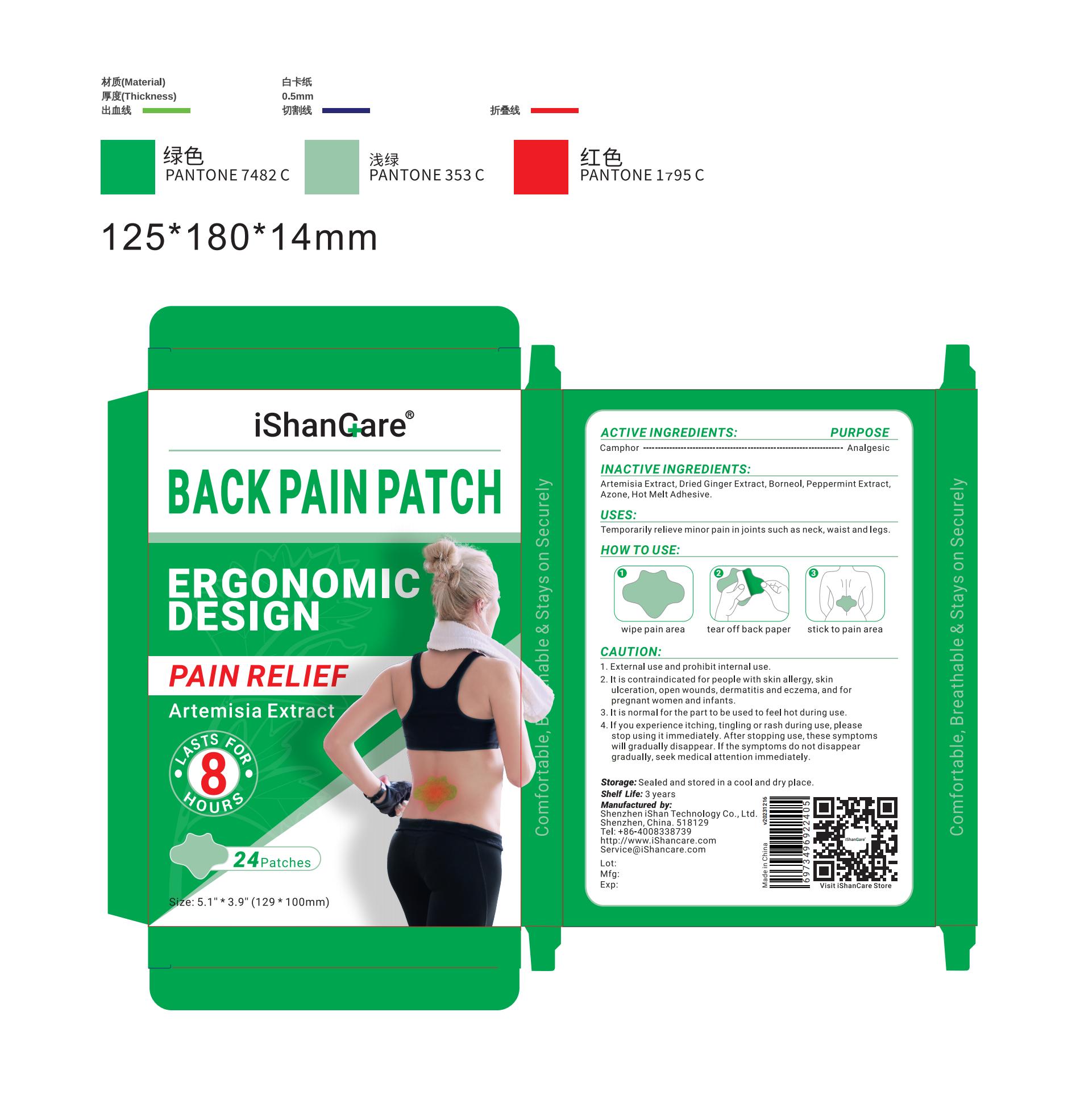 DRUG LABEL: iShancare Back Pain Patch
NDC: 73076-172 | Form: PATCH
Manufacturer: Shenzhen Ishan Technology Co., Ltd
Category: otc | Type: HUMAN OTC DRUG LABEL
Date: 20260212

ACTIVE INGREDIENTS: CAMPHOR, (-)- 1 g/100 g
INACTIVE INGREDIENTS: ARTEMISIA CINA WHOLE; GINGER; BORNEOL; PEPPERMINT; LAUROCAPRAM

Active ingredients

Camphor -------------------------- Analgesic

Inactive Ingredients

Artemisia Extract, Dried Ginger Extract, Borneol, Peppermint Extract,
Azone, Hot Melt Adhesive.

Keep out of reach of children

if swallowed, call poison control or seek medical help.

Stop use

For people with skin allergy, skin ulceration, open wounds, dermatitis and eczema,
and pregnant women, infants.

If you experience itching, tingling or rash during use.

Uses

Temporarily relieve minor pain in joints such as neck, waist and legs.

Other information

Sealed and stored in a cool and dry place.

Directions

Clean and dry affected area.

Tear off the back paper.

Stick to the affected area.

When using this product

not get into eyes. do not apply to wounds or damaged skin.

Warnings

For external use only

Dosage and administration

One time / area / day.